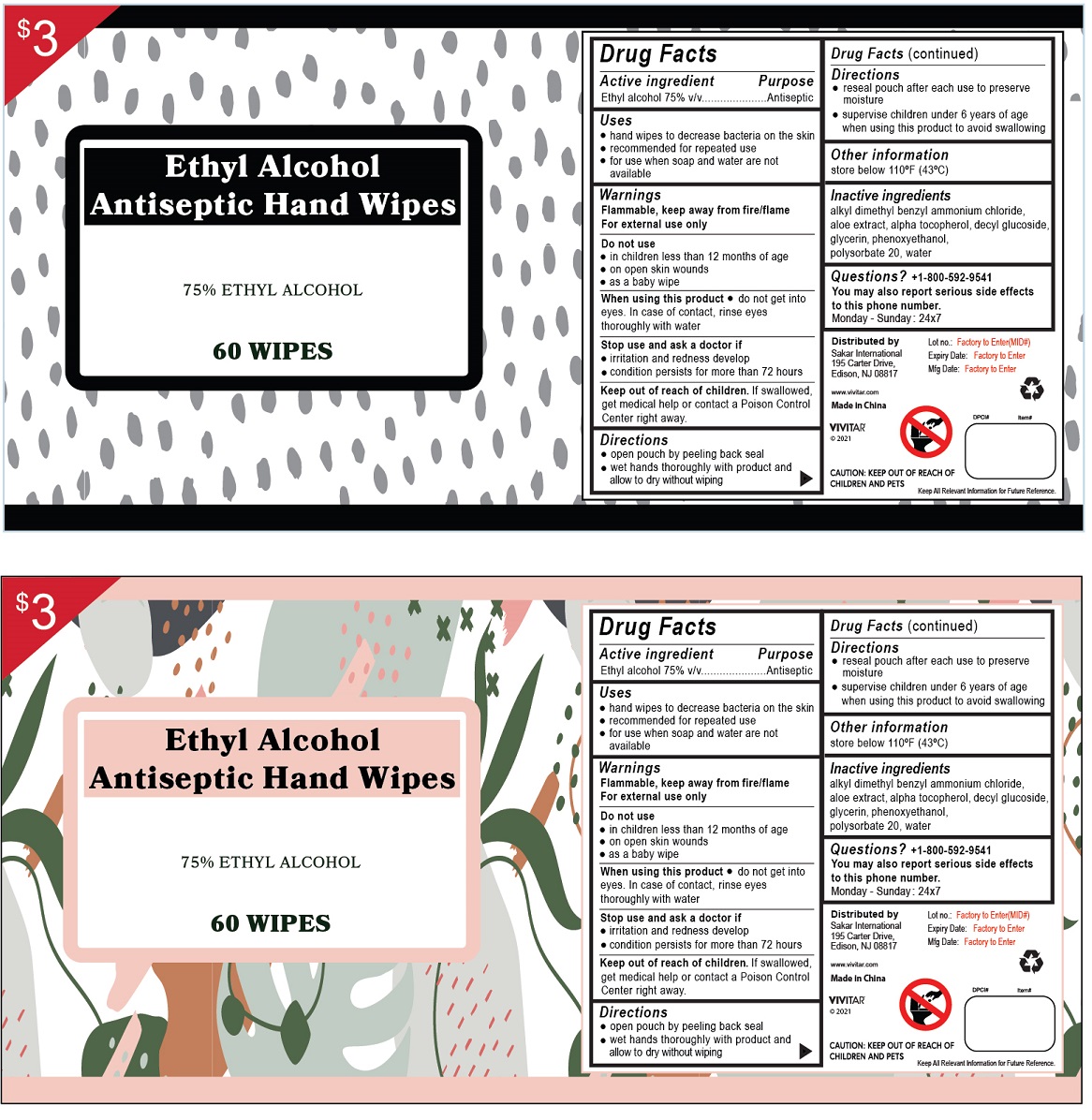 DRUG LABEL: Vivitar Ethyl Alcohol Antiseptic Hand Wipes
NDC: 54826-005 | Form: CLOTH
Manufacturer: Cixi Fanhua Non Woven Products Co., Ltd
Category: otc | Type: HUMAN OTC DRUG LABEL
Date: 20210426

ACTIVE INGREDIENTS: ALCOHOL 75 mL/100 mL
INACTIVE INGREDIENTS: BENZALKONIUM CHLORIDE; ALOE; .ALPHA.-TOCOPHEROL; DECYL GLUCOSIDE; GLYCERIN; PHENOXYETHANOL; POLYSORBATE 20; WATER

Ethyl Alcohol Antiseptic Hand Wipes

Active ingredient

Ethyl alcohol 75% v/v

Purpose

Antiseptic

Uses

• hand wipes to decrease bacteria on the skin
• recommended for repeated use
• for use when soap and water are not available

Warnings

Flammable, keep away from fire/flame
For external use only

Do not use
• in children less than 12 months of age
• on open skin wounds
• as a baby wipe

When using this product • do not get into eyes. In case of contact, rinse eyes thoroughly with water

Stop use and ask a doctor if
• irritation and redness develop
• condition persists for more than 72 hours

Keep out of reach of children. If swallowed, get medical help or contact a Poison Control Center right away.

Directions

• open pouch by peeling back seal
• wet hands thoroughly with product and allow to dry without wiping
• reseal pouch after each use to preserve moisture
• supervise children under 6 years of age when using this product to avoid swallowing

Other information

store below 110ºF (43ºC)

Inactive ingredients

alkyl dimethyl benzyl ammonium chloride, aloe extract, alpha tocopherol, decyl glucoside, glycerin, phenoxyethanol, polysorbate 20, water

Questions? +1-800-592-9541

You may also report serious side effects to this phone number.
Monday - Sunday: 24x7

Distributed by

Sakar International

195 Carter Drive,
Edison, NJ 08817

www.vivitar.com

Made in China

VIVITAR®

©2021

CAUTION : KEEP OUT OF REACH OF CHILDREN AND PETS.

Keep All Relevant Information for Future Reference.